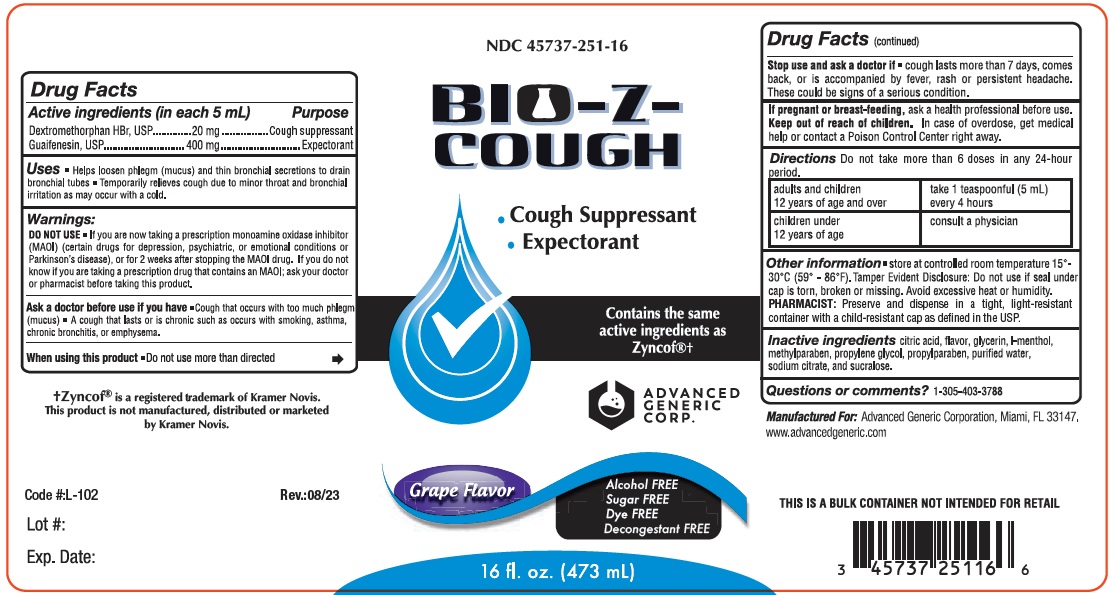 DRUG LABEL: Bio-Z-Cough
NDC: 45737-251 | Form: LIQUID
Manufacturer: Advanced Generic Corporation
Category: otc | Type: HUMAN OTC DRUG LABEL
Date: 20251231

ACTIVE INGREDIENTS: DEXTROMETHORPHAN HYDROBROMIDE 20 mg/5 mL; GUAIFENESIN 400 mg/5 mL
INACTIVE INGREDIENTS: MENTHOL; METHYLPARABEN; PROPYLPARABEN; SUCRALOSE; WATER; PROPYLENE GLYCOL; SODIUM CITRATE; CITRIC ACID MONOHYDRATE

AGC-BioZCough 251

Active Ingredients (in each 5 mL tps.) Purpose

Dextromethorphan Hydrobromide.... 20 mg...........................Cough suppressant

Guaifenesin.... 400 mg........................................................Expectorant

Uses:

- Helps loosen phlegm (mucus) and thin bronchial secretions to drain bronchial tubes.
- Temporarily relieves cough due to minor throat and bronchial irritation as may occur with a cold.

Warnings:

Ask a doctor before use if you have:

- cough that occurs with too much phlegm (mucus)

- cough that lasts or is chronic such as occurs with smoking, asthma, chronic bronchitis, or emphysema.

When using this product do not use more than directed.

Stop use and ask a doctor before use if:

- cough lasts more than 7 days, comes back, or is accompanied by fever, rash or persistent headache. These could be signs of a serious condition.

Do not use:

If you are now taking a prescription monoamine oxidase inhibitor (MAOI) (certain drugs of depression, psychiatric, or emotional conditions or Parkinson's disease), or for 2 weeks after stopping the MAOI drug. If you do not know if you are taking a prescription drug that contains MAOI; ask your doctor or pharmacist before taking this product.

KEEP OUT OF REACH OF CHILDREN

Keep out of the reach of children.In case of overdose, get medical help or contact a Poison Control Center right away.

PREGNANCY OR BREAST FEEDING

If pregnant or breast-feeding,ask a health professional before use.

DOSAGE AND ADMINISTRATION

Direction: do not exceed more than 6 doses in any 24 hours period.

Adults and children 12 years of age and over. | Take 1 teaspoonful (5 mL) every 4 hours
Children under 12 years of age. | Consult a physician

Other Information:

- Store at room temperature 15 - 30 degrees celsius (59 - 86 degrees farenheit)
- Tamper evident feature Do not use if seal under cap is torn, broken or missing.
- Avoid excessive heat or humidity.

Inactive Ingredients:

Citric Acid, flavor, glycerin, menthol, methylparaben, propylene glycol, propylparaben, purified water, sodium citrate, and sucralose

Questions or comments?1-305-403-3788

Manufactured for: Advanced Generic Corporation
Miami, FL 33166

www.advancedgeneric.com